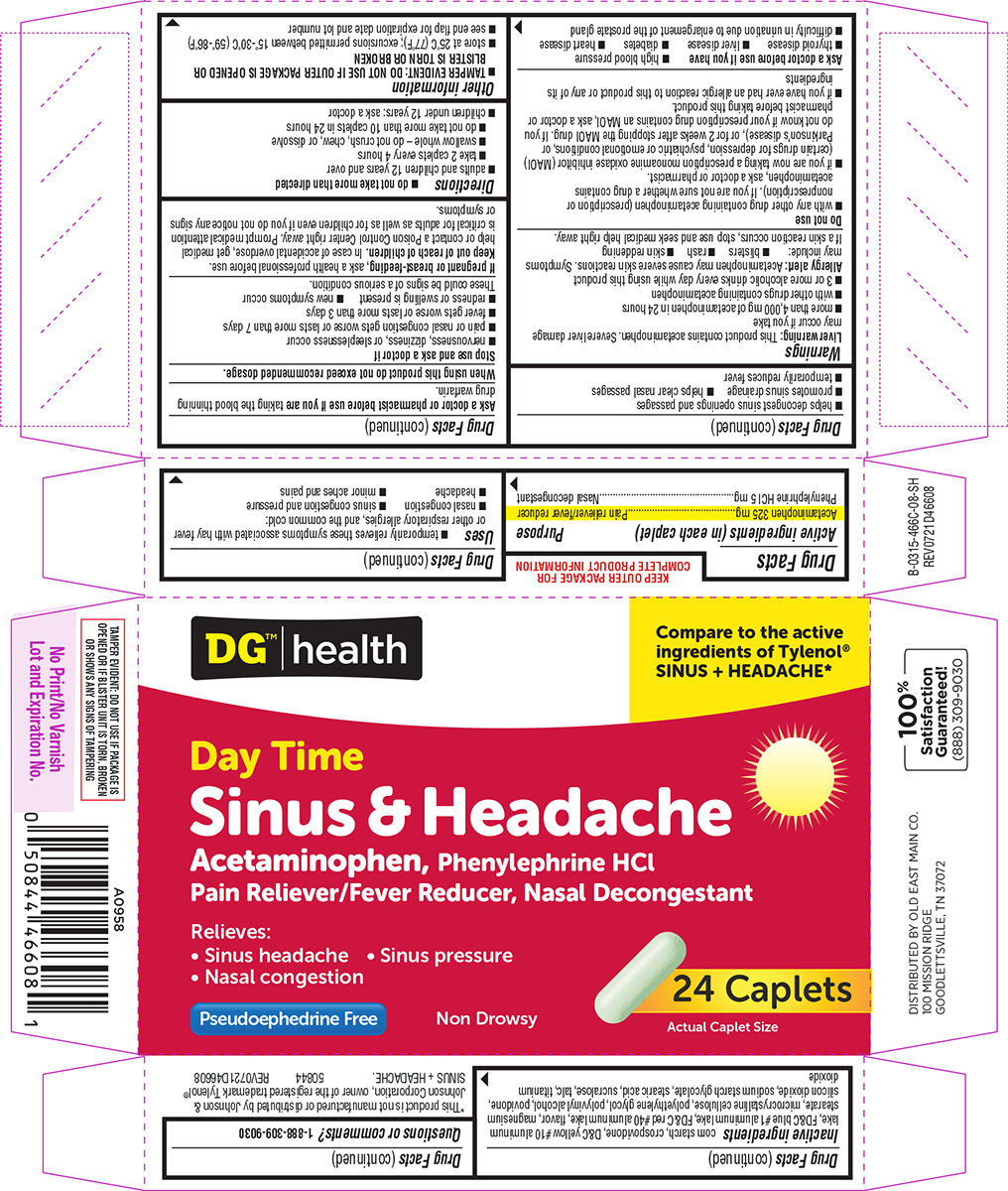 DRUG LABEL: Sinus and Headache
NDC: 55910-466 | Form: TABLET, FILM COATED
Manufacturer: DOLGENCORP, LLC
Category: otc | Type: HUMAN OTC DRUG LABEL
Date: 20260210

ACTIVE INGREDIENTS: ACETAMINOPHEN 325 mg/1 1; PHENYLEPHRINE HYDROCHLORIDE 5 mg/1 1
INACTIVE INGREDIENTS: STARCH, CORN; CROSPOVIDONE, UNSPECIFIED; D&C YELLOW NO. 10 ALUMINUM LAKE; FD&C BLUE NO. 1 ALUMINUM LAKE; FD&C RED NO. 40 ALUMINUM LAKE; MAGNESIUM STEARATE; MICROCRYSTALLINE CELLULOSE; POLYETHYLENE GLYCOL, UNSPECIFIED; POLYVINYL ALCOHOL, UNSPECIFIED; POVIDONE, UNSPECIFIED; SILICON DIOXIDE; SODIUM STARCH GLYCOLATE TYPE A POTATO; STEARIC ACID; SUCRALOSE; TALC; TITANIUM DIOXIDE

Dollar General 44-466C-SH

Active ingredients (in each caplet)

Acetaminophen 325 mg
Phenylephrine HCl 5 mg

Purpose

Pain reliever/fever reducer
Nasal decongestant

Uses

- temporarily relieves these symptoms associated with hay fever or other respiratory allergies, and the common cold:
  - nasal congestion
  - sinus congestion and pressure
  - headache
  - minor aches and pains
- helps decongest sinus openings and passages
- promotes sinus drainage
- helps clear nasal passages
- temporarily reduces fever

Warnings

Liver warning: This product contains acetaminophen. Severe liver damage may occur if you take

- more than 4,000 mg of acetaminophen in 24 hours
- with other drugs containing acetaminophen
- 3 or more alcoholic drinks every day while using this product

Allergy alert: Acetaminophen may cause severe skin reactions. Symptoms may include:

- blisters
- rash
- skin reddening

If a skin reaction occurs, stop use and seek medical help right away.

Do not use

- with any other drug containing acetaminophen (prescription or nonprescription). If you are not sure whether a drug contains acetaminophen, ask a doctor or pharmacist.
- if you are now taking a prescription monoamine oxidase inhibitor (MAOI) (certain drugs for depression, psychiatric or emotional conditions, or Parkinson's disease), or for 2 weeks after stopping the MAOI drug. If you do not know if your prescription drug contains an MAOI, ask a doctor or pharmacist before taking this product.
- if you have ever had an allergic reaction to this product or any of its ingredients

Ask a doctor before use if you have

- high blood pressure
- thyroid disease
- liver disease
- diabetes
- heart disease
- difficulty in urination due to enlargement of the prostate gland

Ask a doctor or pharmacist before use if you are

taking the blood thinning drug warfarin.

When using this product

do not exceed recommended dosage.

Stop use and ask a doctor if

- nervousness, dizziness, or sleeplessness occur
- pain or nasal congestion gets worse or lasts more than 7 days
- fever gets worse or lasts more than 3 days
- redness or swelling is present
- new symptoms occur

These could be signs of a serious condition.

If pregnant or breast-feeding,

ask a health professional before use.

Keep out of reach of children.

In case of accidental overdose, get medical help or contact a Poison Control Center right away. Prompt medical attention is critical for adults as well as for children even if you do not notice any signs or symptoms.

Directions

- do not take more than directed
- adults and children 12 years and over
  - take 2 caplets every 4 hours
  - swallow whole - do not crush, chew, or dissolve
  - do not take more than 10 caplets in 24 hours
- children under 12 years: ask a doctor

Other information

- TAMPER EVIDENT: DO NOT USE IF OUTER PACKAGE IS OPENED OR BLISTER IS TORN OR BROKEN
- store at 25ºC (77ºF); excursions permitted between 15º-30ºC (59º-86ºF)
- see end flap for expiration date and lot number

Inactive ingredients

corn starch, crospovidone, D&C yellow #10 aluminum lake, FD&C blue #1 aluminum lake, FD&C red #40 aluminum lake, flavor, magnesium stearate, microcrystalline cellulose, polyethylene glycol, polyvinyl alcohol, povidone, silicon dioxide, sodium starch glycolate, stearic acid, sucralose, talc, titanium dioxide

Questions or comments?

1-888-309-9030

Principal Display Panel

DG™ | health

Compare to the active
ingredients of Tylenol®
SINUS + HEADACHE*

Day Time
Sinus & Headache

Acetaminophen, Phenylephrine HCl
Pain Reliever/Fever Reducer, Nasal Decongestant

Relieves:
• Sinus headache • Sinus pressure
• Nasal congestion

Pseudoephedrine Free

Non Drowsy

24 Caplets

Actual Caplet Size

TAMPER EVIDENT: DO NOT USE IF PACKAGE IS
OPENED OR IF BLISTER UNIT IS TORN, BROKEN
OR SHOWS ANY SIGNS OF TAMPERING

*This product is not manufactured or distributed by Johnson &
Johnson Corporation, owner of the registered trademark Tylenol®
SINUS + HEADACHE. 50844 REV0721D46608

DISTRIBUTED BY OLD EAST MAIN CO.
100 MISSION RIDGE
GOODLETTSVILLE, TN 37072

100%
Satisfaction
Guaranteed!
(888) 309-9030

Dollar General 44-466C